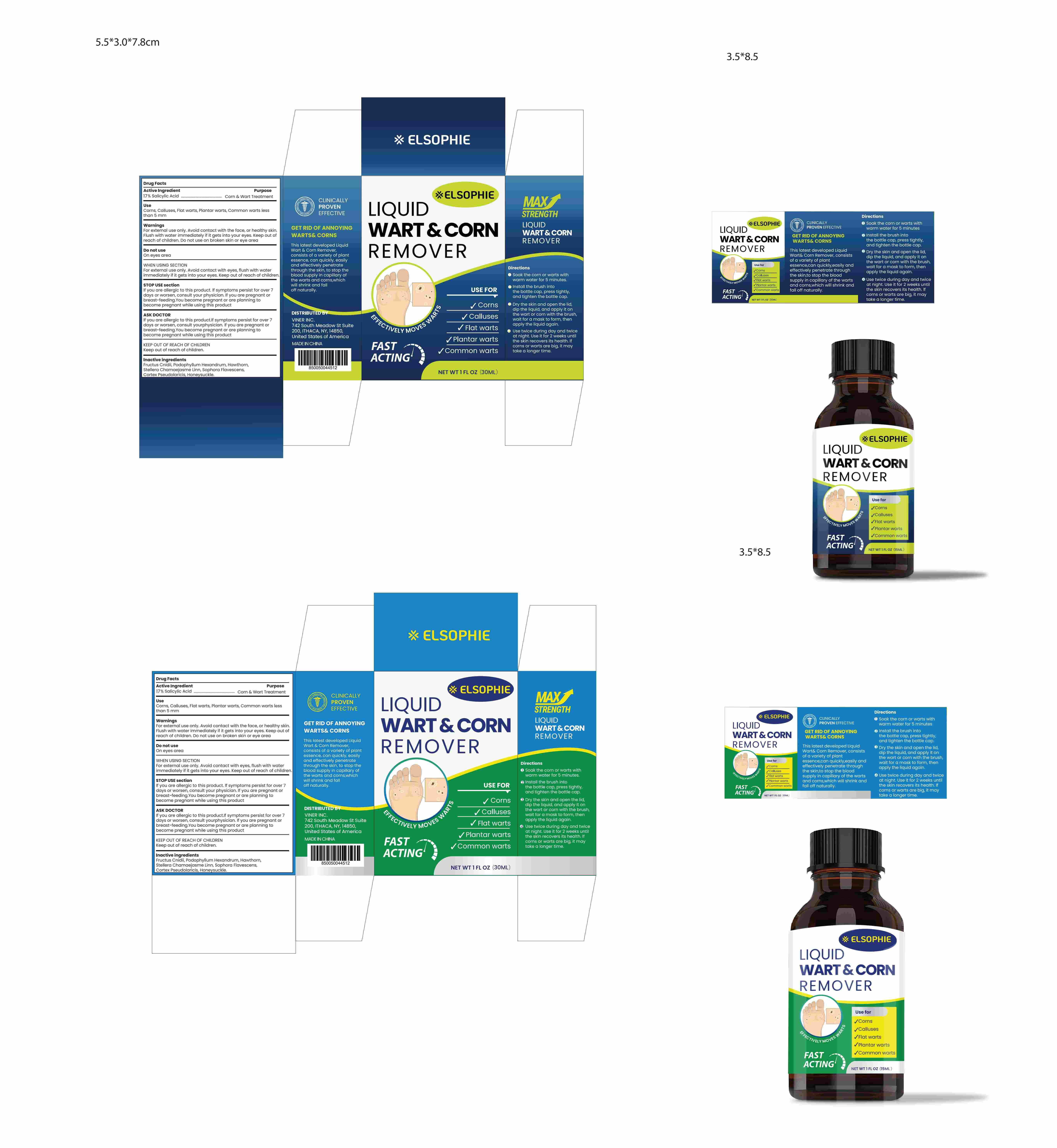 DRUG LABEL: Elsophie Wart Corn Remover
NDC: 83818-021 | Form: LIQUID
Manufacturer: Shenzhen Xinxin Yunhai Technology Co., Ltd.
Category: otc | Type: HUMAN OTC DRUG LABEL
Date: 20250729

ACTIVE INGREDIENTS: SALICYLIC ACID 17 g/100 mL
INACTIVE INGREDIENTS: RUBUS CHINGII WHOLE; PODOPHYLLUM HEXANDRUM WHOLE; AQUILEGIA CANADENSIS WHOLE; STELLERA CHAMAEJASME WHOLE; SOPHORA FLAVESCENS ROOT; CRATAEGUS MONOGYNA FLOWER; PSEUDOLARIX AMABILIS BARK

83818-021

Active Ingredient

salicylic acid 17%

Purpose

corn wart treatment

Use

Corns, calluses, flat warts, plantar warts, common warts less than 5 mm

Warnings

For external use only, avoid contact with the face or healthy skin, flush with water immediately of it gets into your eyes.

Do not use

on eyes area

When Using

for external use only, avoid contact with the face or healthy skin, flush with water immediately of it gets into your eyes.

Stop Use

If you are allergic to this product, if symptoms persist for over 7 days or worsen,consult your physicaian.

Ask Doctor

If you are allergic to this product, if symptoms persist for over 7 days or worsen,consult your physicaian.

Keep Out Of Reach Of Children

Directions

soak the corn warts with warm water for 5 minutes, install the brush into the bottle cap,press tightly, dry the skin and open the lid, dip the liquid and applyu it on the wart or corn with the brush wait for a mask to form then apply the liquid again. use twice during day and twice at night, use it for 2 weeks unbtil the skin recover its health. if corns or warts are big, it may take a long time

Other information

Store at room temperature (15–30°C/59–86°F).

Avoid exposure to direct sunlight or excessive heat.

Inactive ingredients

Fructus cnidii, podophyllum hexandrum, hawthorn, stellera chamaejasme linn, sophora flavescens，Cortex Pseudolaricis，Honeysuckle

Questions

For more information, contact VINER INC. at:

Address: 742 South Meadow St, Suite 200, Ithaca, NY 14850, USA.